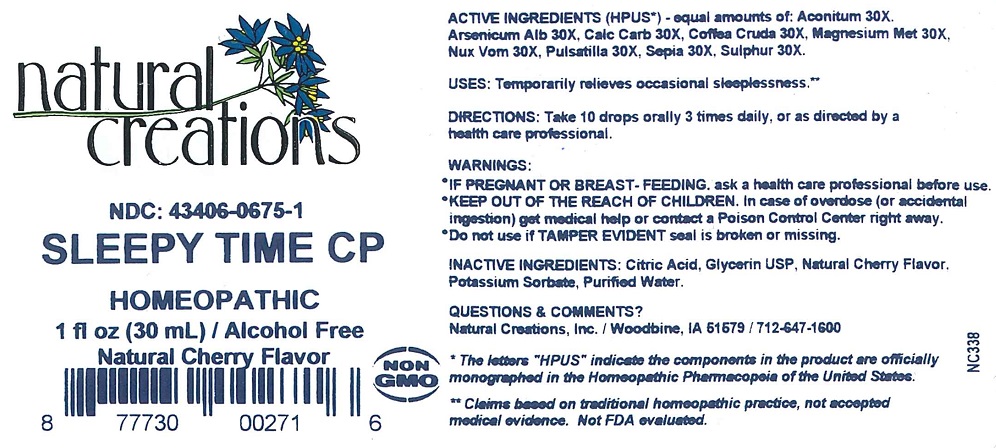 DRUG LABEL: Sleepy Time CP
NDC: 43406-0675 | Form: LIQUID
Manufacturer: Natural Creations, Inc
Category: homeopathic | Type: HUMAN OTC DRUG LABEL
Date: 20251216

ACTIVE INGREDIENTS: ACONITUM NAPELLUS WHOLE 30 [hp_X]/1 mL; ARSENIC TRIOXIDE 30 [hp_X]/1 mL; OYSTER SHELL CALCIUM CARBONATE, CRUDE 30 [hp_X]/1 mL; ARABICA COFFEE BEAN 30 [hp_X]/1 mL; MAGNESIUM 30 [hp_X]/1 mL; STRYCHNOS NUX-VOMICA SEED 30 [hp_X]/1 mL; PULSATILLA VULGARIS WHOLE 30 [hp_X]/1 mL; SEPIA OFFICINALIS JUICE 30 [hp_X]/1 mL; SULFUR 30 [hp_X]/1 mL
INACTIVE INGREDIENTS: CITRIC ACID MONOHYDRATE; GLYCERIN; POTASSIUM SORBATE; WATER

Sleepy Time CP

ACTIVE INGREDIENT

ACTIVE INGREDIENTS (HPUS*) - equal amounts of: Aconitum 30X, Arsenicum Alb 30X, Calc Carb 30X, Coffea Cruda 30X, Magnesium Met 30X, Nux Vom 30X, Pulsatilla 30X, Sepia 30X, Sulphur 30X

INDICATIONS AND USAGE

USES: Temporarily relieves occasional sleeplessness.**

PURPOSE

USES: Temporarily relieves occasional sleeplessness.**

DOSAGE AND ADMINISTRATION

DIRECTIONS: Adults & children above 12 years: 10 drops orally 3 times daily, or as directed by a health care professional.

KEEP OUT OF REACH OF CHILDREN

KEEP OUT OF THE REACH OF CHILDREN. In case of overdose (or accidental ingestion) get medical help or contact a Poison Control Center right away.

WARNINGS:

- IF PREGNANT OR BREAST-FEEDING, ask a health care professional before use.
- KEEP OUT OF THE REACH OF CHILDREN. In case of overdose (or accidental ingestion) get medical help or contact a Poison Control Center right away.
- Do not use if TAMPER EVIDENT seal is broken or missing.

INACTIVE INGREDIENT

INACTIVE INGREDIENTS: Citric Acid, Glycerin USP, Natural Cherry Flavor, Potassium Sorbate, Purified Water

QUESTIONS & COMMENTS?

Natural Creations, Inc. / Woodbine, IA 51579 / 712-647-1600

REFERENCES

*The letters "HPUS" indicate the components in the product are officially monographed in the Homeopathic Pharmacopeia of the United States.

**Claims based on traditional homeopathic practice, not accepted medical evidence. Not FDA evaluated.

PACKAGE LABEL

NDC:43406-0675-1

Sleepy Time CP

HOMEOPATHIC

1 fl oz (30mL) / Alcohol Free